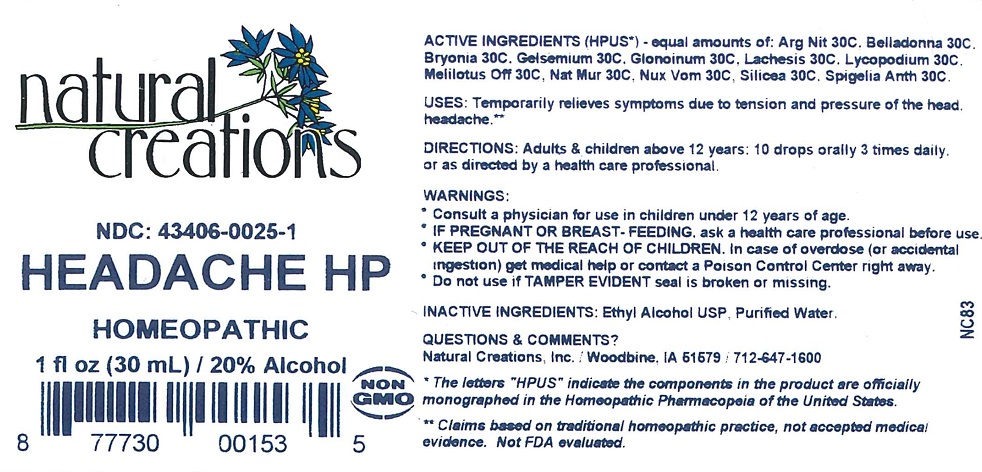 DRUG LABEL: HEADACHE HP
NDC: 43406-0025 | Form: LIQUID
Manufacturer: Natural Creations, Inc.
Category: homeopathic | Type: HUMAN OTC DRUG LABEL
Date: 20251212

ACTIVE INGREDIENTS: SILVER NITRATE 30 [hp_C]/1 mL; ATROPA BELLADONNA 30 [hp_C]/1 mL; BRYONIA ALBA ROOT 30 [hp_C]/1 mL; NITROGLYCERIN 30 [hp_C]/1 mL; LACHESIS MUTA VENOM 30 [hp_C]/1 mL; LYCOPODIUM CLAVATUM SPORE 30 [hp_C]/1 mL; MELILOTUS OFFICINALIS TOP 30 [hp_C]/1 mL; SODIUM CHLORIDE 30 [hp_C]/1 mL; STRYCHNOS NUX-VOMICA SEED 30 [hp_C]/1 mL; SILICON DIOXIDE 30 [hp_C]/1 mL; SPIGELIA ANTHELMIA 30 [hp_C]/1 mL
INACTIVE INGREDIENTS: WATER; ALCOHOL

HEADACHE HP

ACTIVE INGREDIENT

ACTIVE INGREDIENTS (HPUS*): Argentum Nitricum 30C, Belladonna 30C, Bryonia Alba 30C, Gelsemium Sempervirens 30C, Glonoinum 30C, Lachesis Mutus 30C, Lycopodium Clavatum 30C, Melilotus Officinalis 30C, Natrum Muriaticum 30C, Nux Vomica 30C, Silicea 30C, Spigelia Anthelmia 30C

INDICATIONS AND USAGE

USES: Temporarily relieves symptoms due to tension and pressure of the head, headache.**

WARNING:

- Consult a physician for use in children under 12 years of age.
- IF PREGNANT OR BREAST-FEEDING, ask a health care professional before use.
- KEEP OUT OF THE REACH OF CHILDREN. In case of overdose (or accidental ingestion) get medical help or contact a Poison Control Center right away.
- DO not use if TAMPER EVIDENT seal is broken or missing.

DOSAGE AND ADMINISTRATION

DIRECTIONS: Adults and children above 12 years: 10 drops orally 3 times daily, or as directed by a health care professional.

REFERENCES

*The letters "HPUS" indicate the components in the product are officially monographed in the Homeopathic Pharmacopeia of the United States.

**Claims based on traditional homeopathic practice, not accepted medical evidence. Not FDA evaluated.

INACTIVE INGREDIENTS: Purified Water, USP Ethyl Alcohol

QUESTIONS AND COMMENTS?

Natural Creations / Woodbine, IA / 51579 / 712-647-1600

PURPOSE

USES: Temporarily relieves symptoms due to tension and pressure of the head, headache.**

KEEP OUT OF REACH OF CHILDREN

KEEP OUT OF THE REACH OF CHILDREN. In case of overdose (or accidental ingestion) get medical help or contact a Poison Control Center.

PACKAGE LABEL

NDC: 43406-0025-1

HEADACHE HP

HOMEOPATHIC

1 fl oz (30mL) / 20% Alcohol